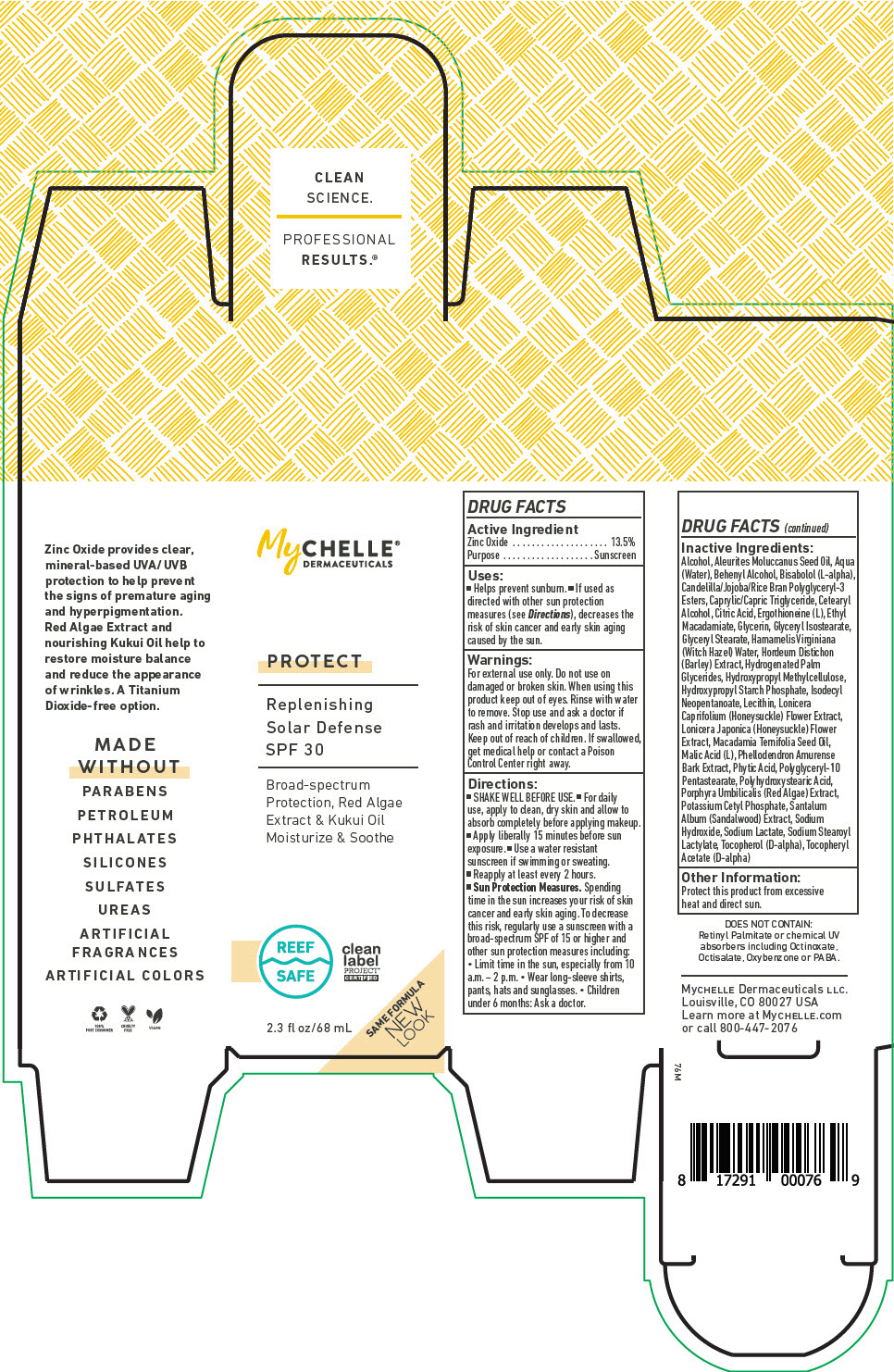 DRUG LABEL: MyChelle Dermaceuticals Replenishing Solar Defense SPF 30 
NDC: 72805-031 | Form: LOTION
Manufacturer: French Transit, Ltd.
Category: otc | Type: HUMAN OTC DRUG LABEL
Date: 20220106

ACTIVE INGREDIENTS: Zinc Oxide 13.5 g/100 mL
INACTIVE INGREDIENTS: WATER; Alcohol; KUKUI NUT OIL; DOCOSANOL; LEVOMENOL; MEDIUM-CHAIN TRIGLYCERIDES; CETOSTEARYL ALCOHOL; ANHYDROUS CITRIC ACID; ERGOTHIONEINE; Ethyl Macadamiate; Glycerin; Glyceryl Isostearate; GLYCERYL MONOSTEARATE; HAMAMELIS VIRGINIANA TOP WATER; BARLEY; Hydrogenated Palm Glycerides; HYPROMELLOSE, UNSPECIFIED; HYDROXYPROPYL DISTARCH PHOSPHATE, HIGH AMYLOSE CORN; Isodecyl Neopentanoate; LECITHIN, SOYBEAN; LONICERA CAPRIFOLIUM FLOWER; LONICERA JAPONICA FLOWER; MACADAMIA OIL; MALIC ACID, L-; PHELLODENDRON AMURENSE BARK; FYTIC ACID; Polyglyceryl-10 Pentastearate; POLYHYDROXYSTEARIC ACID (2300 MW); PORPHYRA UMBILICALIS; Potassium Cetyl Phosphate; SANDALWOOD; Sodium Hydroxide; Sodium Lactate; Sodium Stearoyl Lactylate; .ALPHA.-TOCOPHEROL, D-; .ALPHA.-TOCOPHEROL ACETATE, D-

MyChelle® Dermaceuticals Replenishing Solar Defense SPF 30
Protect

DRUG FACTS

Active Ingredient

Zinc Oxide 13.5%

Purpose

Sunscreen

Uses

- Helps prevent sunburn.
- If used as directed with other sun protection measures (see Directions), decreases the risk of skin cancer and early skin aging caused by the sun.

Warnings

For external use only. Do not use on damaged or broken skin. When using this product keep out of eyes. Rinse with water to remove. Stop use and ask a doctor if rash and irritation develops and lasts.

Keep out of reach of children. If swallowed, get medical help or contact a Poison Control Center right away.

Directions

- SHAKE WELL BEFORE USE.
- For daily use, apply to clean, dry skin and allow to absorb completely before applying makeup.
- Apply liberally 15 minutes before sun exposure.
- Use a water resistant sunscreen if swimming or sweating.
- Reapply at least every 2 hours.
- Sun Protection Measures. Spending time in the sun increases your risk of skin cancer and early skin aging. To decrease this risk, regularly use a sunscreen with a broad-spectrum SPF of 15 or higher and other sun protection measures including:
  - Limit time in the sun, especially from 10 a.m. – 2 p.m.
  - Wear long-sleeve shirts, pants, hats and sunglasses.
  - Children under 6 months: Ask a doctor.

Inactive Ingredients

Alcohol, Aleurites Moluccanus Seed Oil, Aqua (Water), Behenyl Alcohol, Bisabolol (L-alpha), Candelilla/Jojoba/Rice Bran Polyglyceryl-3 Esters, Caprylic/Capric Triglyceride, Cetearyl Alcohol, Citric Acid, Ergothioneine (L), Ethyl Macadamiate, Glycerin, Glyceryl Isostearate, Glyceryl Stearate, Hamamelis Virginiana (Witch Hazel) Water, Hordeum Distichon (Barley) Extract, Hydrogenated Palm Glycerides, Hydroxypropyl Methylcellulose, Hydroxypropyl Starch Phosphate, Isodecyl Neopentanoate, Lecithin, Lonicera Caprifolium (Honeysuckle) Flower Extract, Lonicera Japonica (Honeysuckle) Flower Extract, Macadamia Ternifolia Seed Oil, Malic Acid (L), Phellodendron Amurense Bark Extract, Phytic Acid, Polyglyceryl-10 Pentastearate, Polyhydroxystearic Acid, Porphyra Umbilicalis (Red Algae) Extract, Potassium Cetyl Phosphate, Santalum Album (Sandalwood) Extract, Sodium Hydroxide, Sodium Lactate, Sodium Stearoyl Lactylate, Tocopherol (D-alpha), Tocopheryl Acetate (D-alpha)

Other Information

Protect this product from excessive heat and direct sun.

PRINCIPAL DISPLAY PANEL - 68 mL Tube Box

MyCHELLE®
DERMACEUTICALS

PROTECT

Replenishing
Solar Defense
SPF 30

Broad-spectrum
Protection, Red Algae
Extract & Kukui Oil
Moisturize & Soothe

REEF
SAFE

clean
label
PROJECT®
CERTIFIED

2.3 fl oz/68 mL

SAME FORMULA
NEW
LOOK